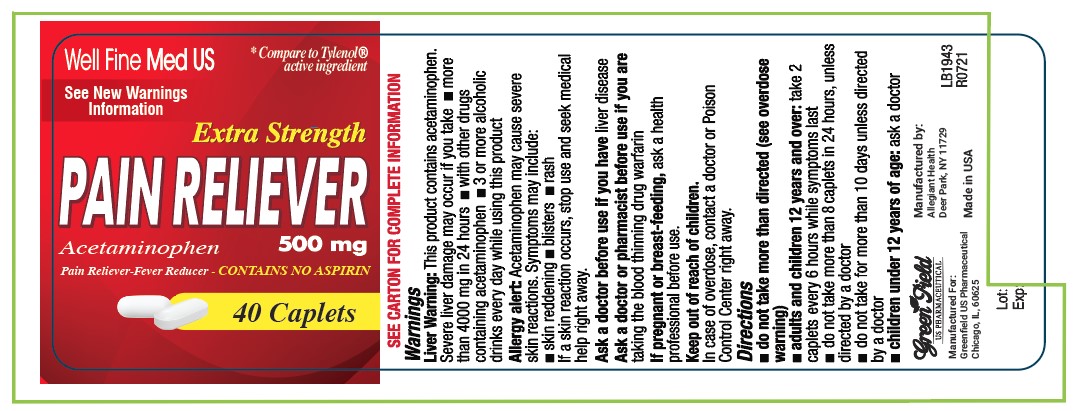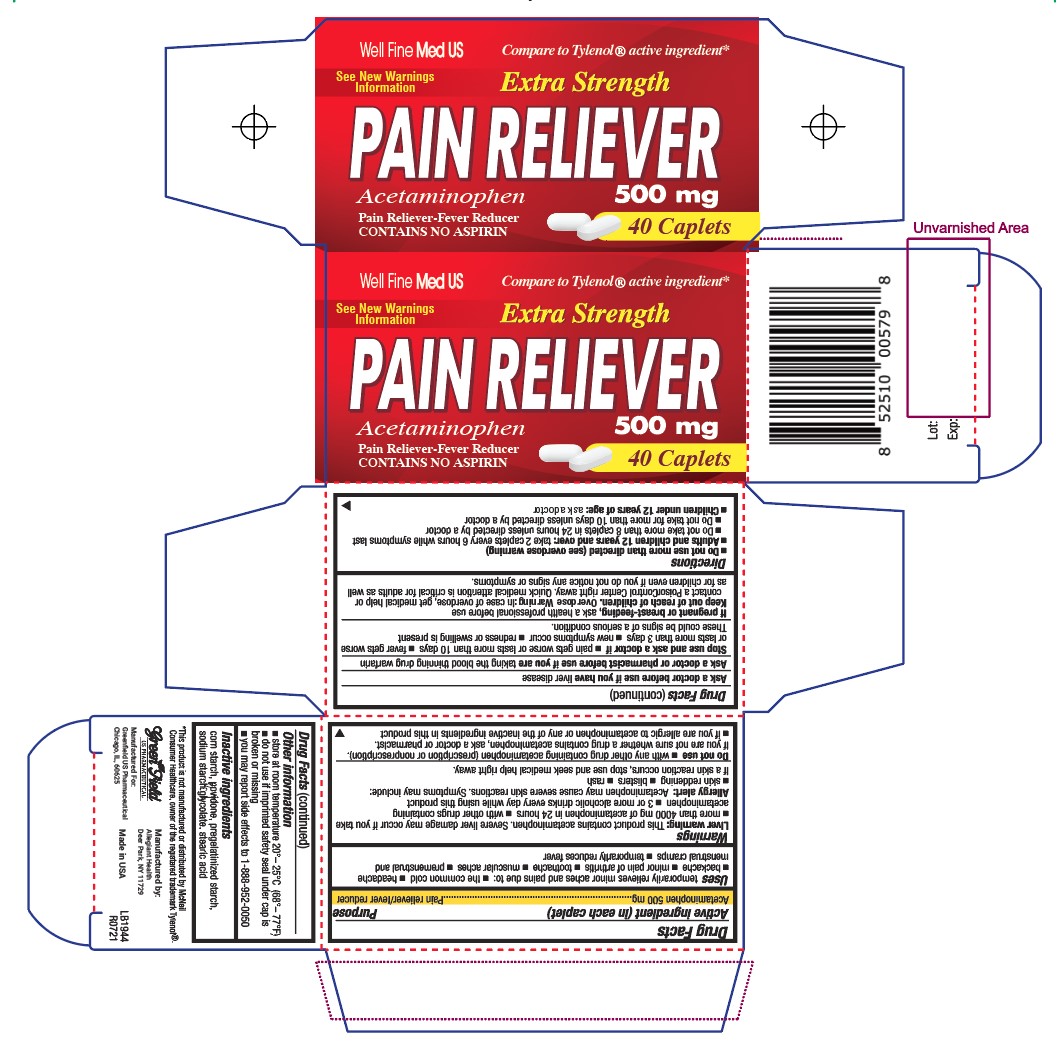 DRUG LABEL: Pain Relief
NDC: 69168-005 | Form: TABLET
Manufacturer: Allegiant Health
Category: otc | Type: HUMAN OTC DRUG LABEL
Date: 20211123

ACTIVE INGREDIENTS: ACETAMINOPHEN 500 mg/1 1
INACTIVE INGREDIENTS: STARCH, CORN; POVIDONE; STEARIC ACID; SODIUM STARCH GLYCOLATE TYPE A CORN

GreenField - Pain Relief

Active ingredient(s)

Acetaminophen 500 mg

Purpose

Pain reliever/fever reducer

Use(s)

temporary relief of minor aches and pains associated with ■ common cold ■ headache ■ toothache

■ muscular aches ■ backache ■ arthritis ■ menstrual cramps ■ and reduction of fever

Warnings

Liver warning: This product contains acetaminophen. Severe liver damage may occur if you take more than 4000 mg of acetaminophen in 24 hours, which is the maximum daily amount with other drugs containing acetaminophen 3 or more alcoholic drinks every day while using this product

Allergy alert: acetaminophen may cause severe skin reactions. Symptoms may include: ■ skin reddening ■ blisters ■ rash
If a skin reaction occurs, stop use and seek medical help right away

Do not use

- with any other drug containing acetaminophen (prescription or nonprescription). If you are not sure whether a
  drug contains acetaminophen, ask a doctor or pharmacist.

- if you are allergic to acetaminophen or any of the inactive ingredients in this product

Ask a doctor before use if

you have liver disease

Ask a doctor or pharmacist before use if

you are taking the blood thinning drug warfarin

Stop use and ask a doctor if

- pain gets worse or lasts more than 10 days

- fever gets worse or lasts more than 3 days

- new symptoms occur

- redness or swelling is present. These could be signs of a serious condition

Pregnancy/Breastfeeding

If pregnant or breast-feeding, ask a health professional before use.

Keep out of reach of children

In case of overdose, get medical help or contact a Poison Control Center right away.
Quick medical attention is critical for adults as well as for children even if you do not notice any signs or symptoms.

Directions

■ do not use more than directed (see overdose warning)

■ adults and children 12 years and over: take 2 caplets every 6 hours while symptoms last

■ Do not take more than 8 caplets in 24 hours unless directed by a doctor

■ Do not use more than 10 days unless directed by a doctor

■ children under 12 years: ask a doctor

Other information

- store between 20º-25ºC (68º-77ºF)
- do not use if imprinted safety seal under cap is broken or missing

- You may report side effects to 1-888-952-0050

Inactive ingredients

corn starch, povidone, pregelatinized starch, sodium starch glycolate, stearic acid

Principal Display Panel

Pain Relief
Pain Relief